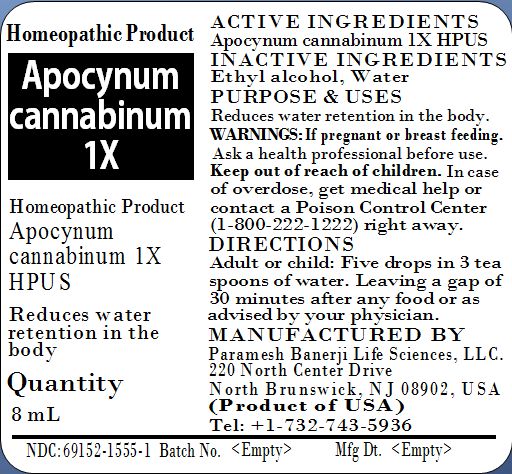 DRUG LABEL: Apocynum cannabinum 1X
NDC: 69152-1555 | Form: LIQUID
Manufacturer: Paramesh Banerji Life Sciences LLC
Category: homeopathic | Type: HUMAN PRESCRIPTION DRUG LABEL
Date: 20150605

ACTIVE INGREDIENTS: APOCYNUM CANNABINUM ROOT 1 [hp_X]/8 mL
INACTIVE INGREDIENTS: ALCOHOL; WATER

Active Ingredients

Apocynum cannabinum 1X HPUS

Inactive Ingredients

Ethyl alcohol, Water

Purpose

Reduces water retention in the body

Uses

Reduces water retention in the body

Warnings

If pregnant or breast feeding ask a health professional before use.

Keep out of reach of children. In case of overdose, get medical help or contact a Poison Control Center (1-800-222-1222) right away.

Direction

Adult or child: Five drops in 3 tea spoons of water, leaving a gap of 30 minutes from any food or as advised by your physician.

Manufactured by

Paramesh Banerji Life Sciences, LLC

220 North Center Drive

North Brunswick, NJ 08902, USA

Product of USA

Tel: +1-732-743-5936

Principal Display Panel

Homeopathic Product

Apocynum cannabinum 1X

Homeopathic Product

Apocynum cannabinum 1X HPUS

Reduces water retention in the body

Quantity

8 mL